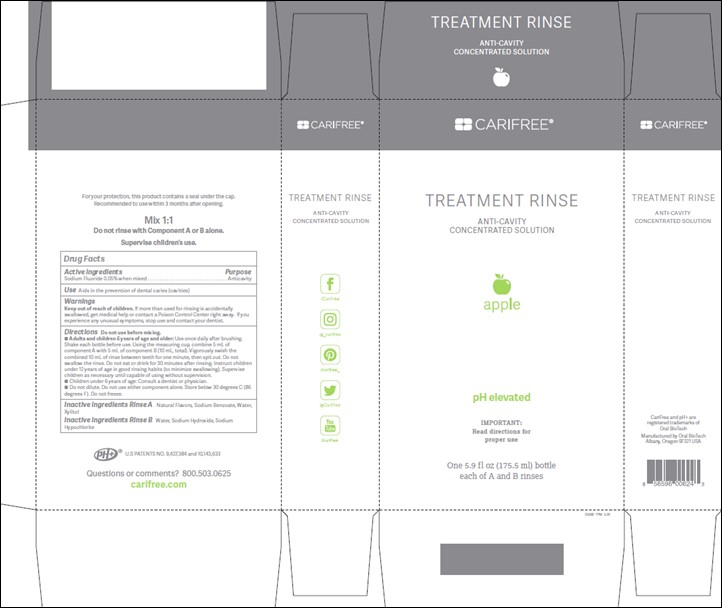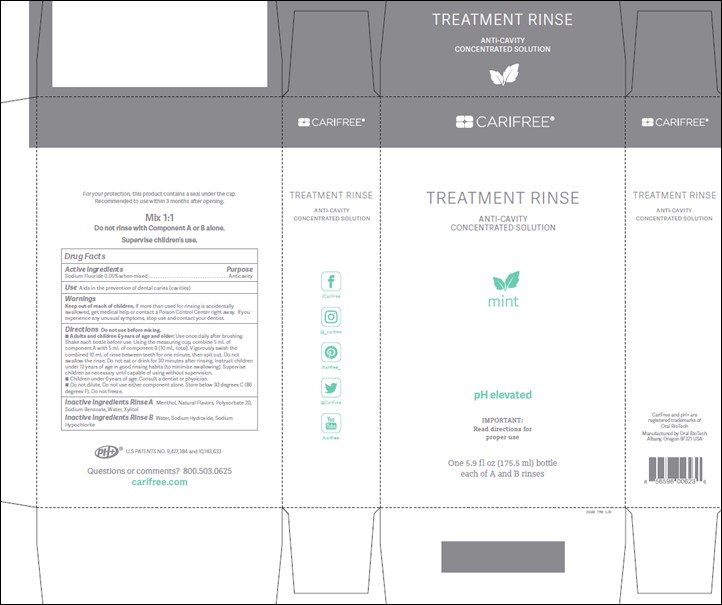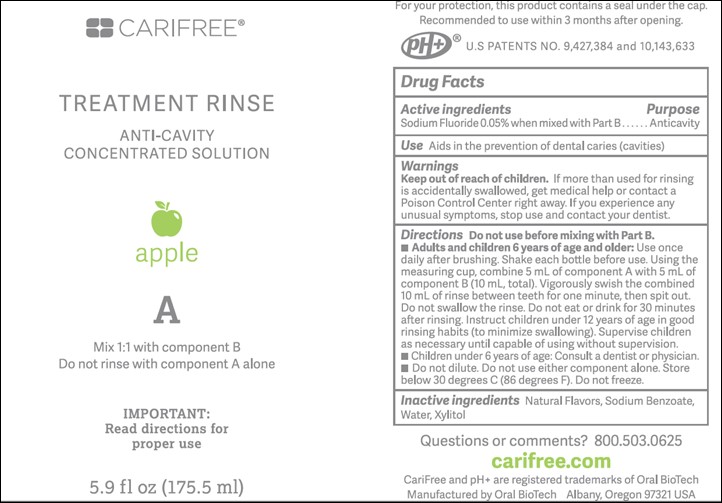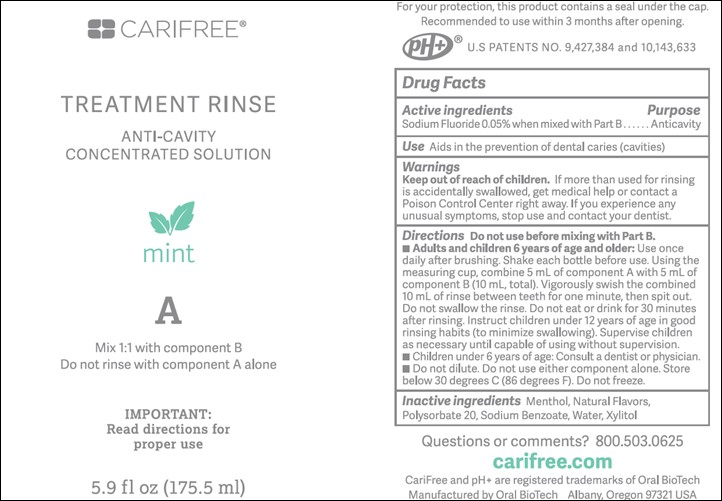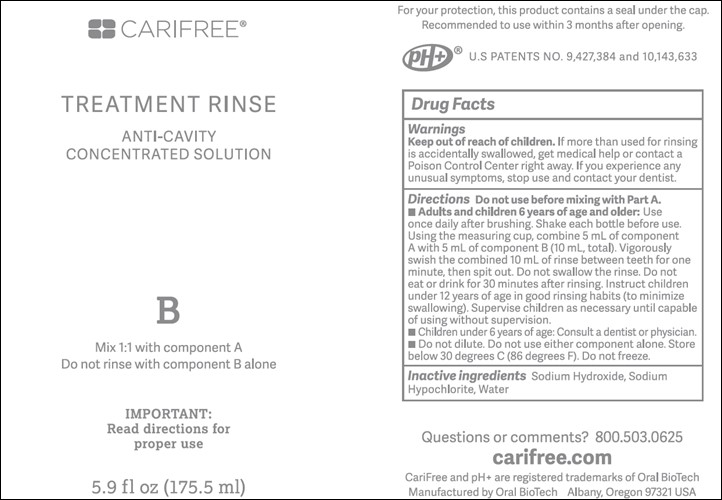 DRUG LABEL: Treatment Rinse
NDC: 61578-315 | Form: RINSE
Manufacturer: DENTAL ALLIANCE HOLDINGS LLC
Category: otc | Type: HUMAN OTC DRUG LABEL
Date: 20240131

ACTIVE INGREDIENTS: SODIUM FLUORIDE 226 ug/1 mL
INACTIVE INGREDIENTS: SODIUM BENZOATE; WATER; XYLITOL; SODIUM HYDROXIDE; SODIUM HYPOCHLORITE

Treatment Rinse

Active ingredients:

Sodium Fluoride 0.05% when mixed with part B

Purpose:

Anticavity

Use:

Aids in the prevention of dental caries (cavities)

Warnings:

Keep out of reach of children. If more than used for rinsing is accidentally swallowed, get medical help or contact a Poison Control Center right away. If you experience any unusual symptoms, stop use and contact your dentist.

Warnings:

Keep out of reach of children.

Directions:

Do not use before mixing with Part B. Adults and children 6 years of age and older: Use once daily after brushing. Shake each bottle before use. Using the measuring cup, combine 5 mL of component A with 5 mL of component B (10 mL, total). Vigorously swish the combined 10 mL of rinse between teeth for one minute, then spit out. Do not swallow the rinse. Do not eat or drink for 30 minutes after rinsing. Instruct children under 12 years of age in good rinsing habits (to minimize swallowing). Supervise children as necessary until capable of using without supervision. Children under 6 years of age: Consult a dentist or physician. Do not dilute. Do not use either component alone. Store below 30 degrees C (86 degrees F). Do not freeze.

Inactive ingredients:

Menthol, Natural Flavors, Polysorbate 20, Sodium Benzoate, Sodium Hydroxide, Sodium Hypochlorite, Water, Xylitol.